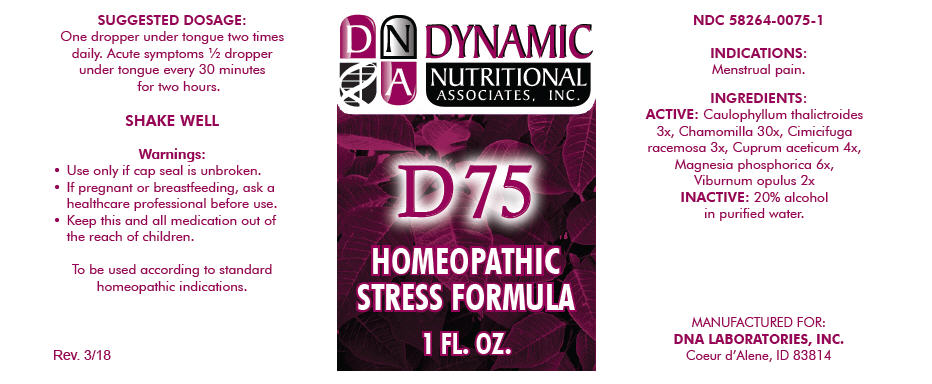 DRUG LABEL: D-75
NDC: 58264-0075 | Form: SOLUTION
Manufacturer: DNA Labs, Inc.
Category: homeopathic | Type: HUMAN OTC DRUG LABEL
Date: 20250113

ACTIVE INGREDIENTS: CAULOPHYLLUM THALICTROIDES ROOT 3 [hp_X]/1 mL; MATRICARIA CHAMOMILLA 30 [hp_X]/1 mL; BLACK COHOSH 3 [hp_X]/1 mL; CUPRIC ACETATE 4 [hp_X]/1 mL; MAGNESIUM PHOSPHATE, DIBASIC TRIHYDRATE 6 [hp_X]/1 mL; VIBURNUM OPULUS BARK 2 [hp_X]/1 mL
INACTIVE INGREDIENTS: ALCOHOL; WATER

D-75

NDC 58264-0075-1

INDICATIONS

PURPOSE

Menstrual pain.

INGREDIENTS

ACTIVE

Caulophyllum thalictroides 3x, Chamomilla 30x, Cimicifuga racemosa 3x, Cuprum aceticum 4x, Magnesia phosphorica 6x, Viburnum opulus 2x

INACTIVE

20% alcohol in purified water.

SUGGESTED DOSAGE

One dropper under tongue two times daily. Acute symptoms ½ dropper under tongue every 30 minutes for two hours.

STORAGE AND HANDLING

SHAKE WELL

Warnings

- Use only if cap seal is unbroken.

PREGNANCY OR BREAST FEEDING

- If pregnant or breastfeeding, ask a healthcare professional before use.

KEEP OUT OF REACH OF CHILDREN

- Keep this and all medication out of the reach of children.

To be used according to standard homeopathic indications.

PRINCIPAL DISPLAY PANEL - 1 FL. OZ. Bottle Label

DYNAMIC
NUTRITIONAL
ASSOCIATES, INC.

D 75

HOMEOPATHIC
STRESS FORMULA

1 FL. OZ.